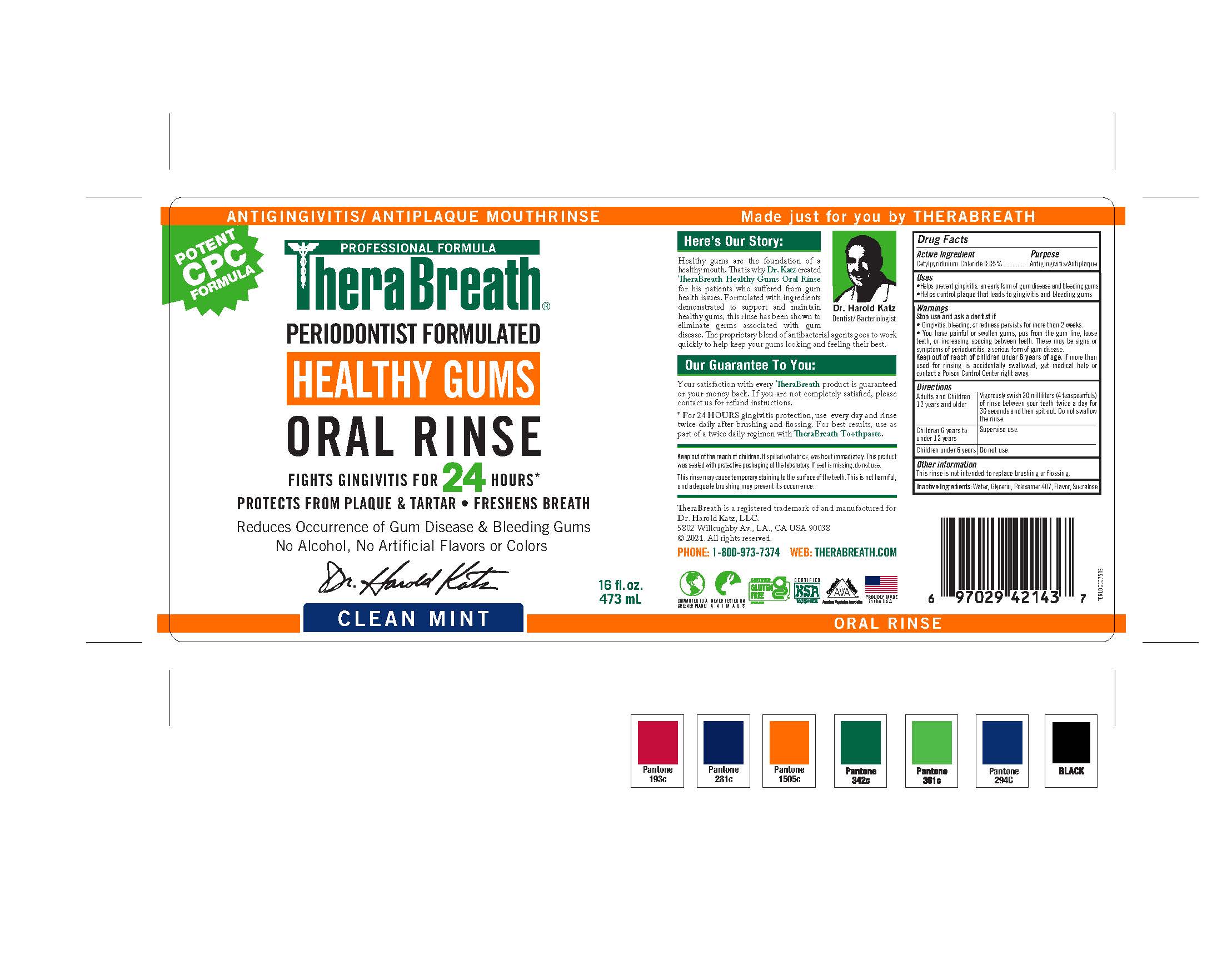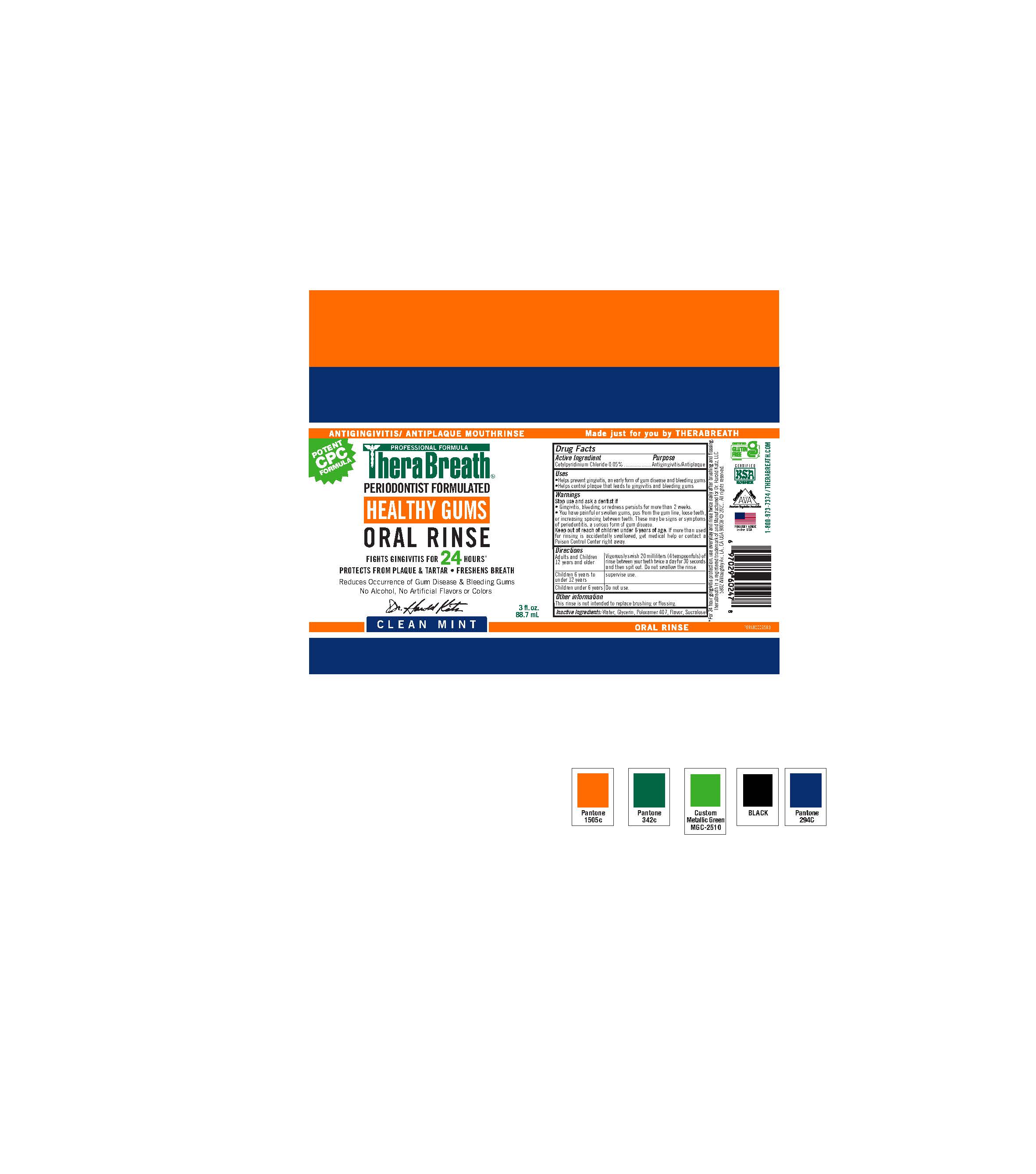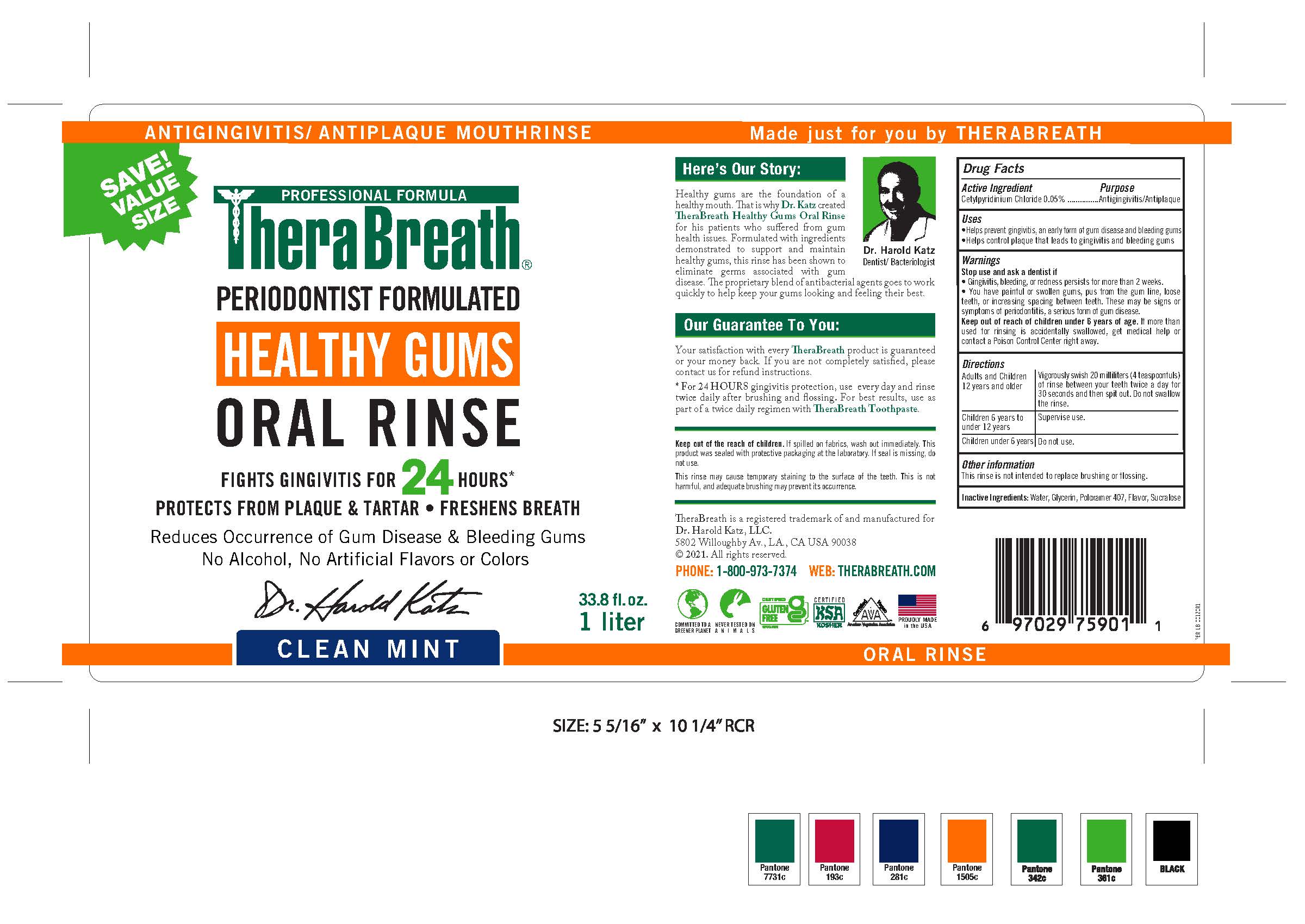 DRUG LABEL: TheraBreath Healthy Gums Oral Rinse
NDC: 72551-247 | Form: RINSE
Manufacturer: Dr. Harold Katz, LLC
Category: otc | Type: HUMAN OTC DRUG LABEL
Date: 20220201

ACTIVE INGREDIENTS: CETYLPYRIDINIUM CHLORIDE 0.0005 g/1 g
INACTIVE INGREDIENTS: POLOXAMER 407; WATER; SUCRALOSE; GLYCERIN

TheraBreath Healthy Gums Oral Rinse

Active Ingredient

Cetylpyridinium chloride 0.05%

Purpose

Antigingivitis/Antiplaque

Uses

•Helps prevent gingivitis, an early form of gum disease and bleeding gum
•Helps control plaque that leads to gingivitis and bleeding gums

Warnings

Keep out of reach of children under 6 years of age. If more than used for rinsing is accidentally swallowed, get medical help or contact a Poison Control Center right away.

Warnings

Stop Use and Ask a Doctor If

- Gingivitis, bleeding, or redness persists for more than 2 weeks.
- You have painful or swollen gums, pus from the gum line, loose teeth, or increasing spacing between teeth. These may or symptoms of periodontitis, a serious form of gum disease.

Directions

Adults and Children 12 years and older | Vigorously swish 20 milliliters (4 teaspoonfuls) of rinse between your teeth; twice a day for 30 seconds and then spit out. Do not swallow the rinse.
Children 6 years to under12 years | supervise use.
Children under 6 years | Do not use.

Other Information

This rinse is not intended to replace brushing or flossing.

Inactive Ingredients

Water, Glycerin, Poloxamer 407, Flavor, Sucralose

TheraBreath Healthy Gums Oral Rinse

72551-247-05

PACKAGE LABEL

72551-247-01

PACKAGE LABEL

72551-247-04